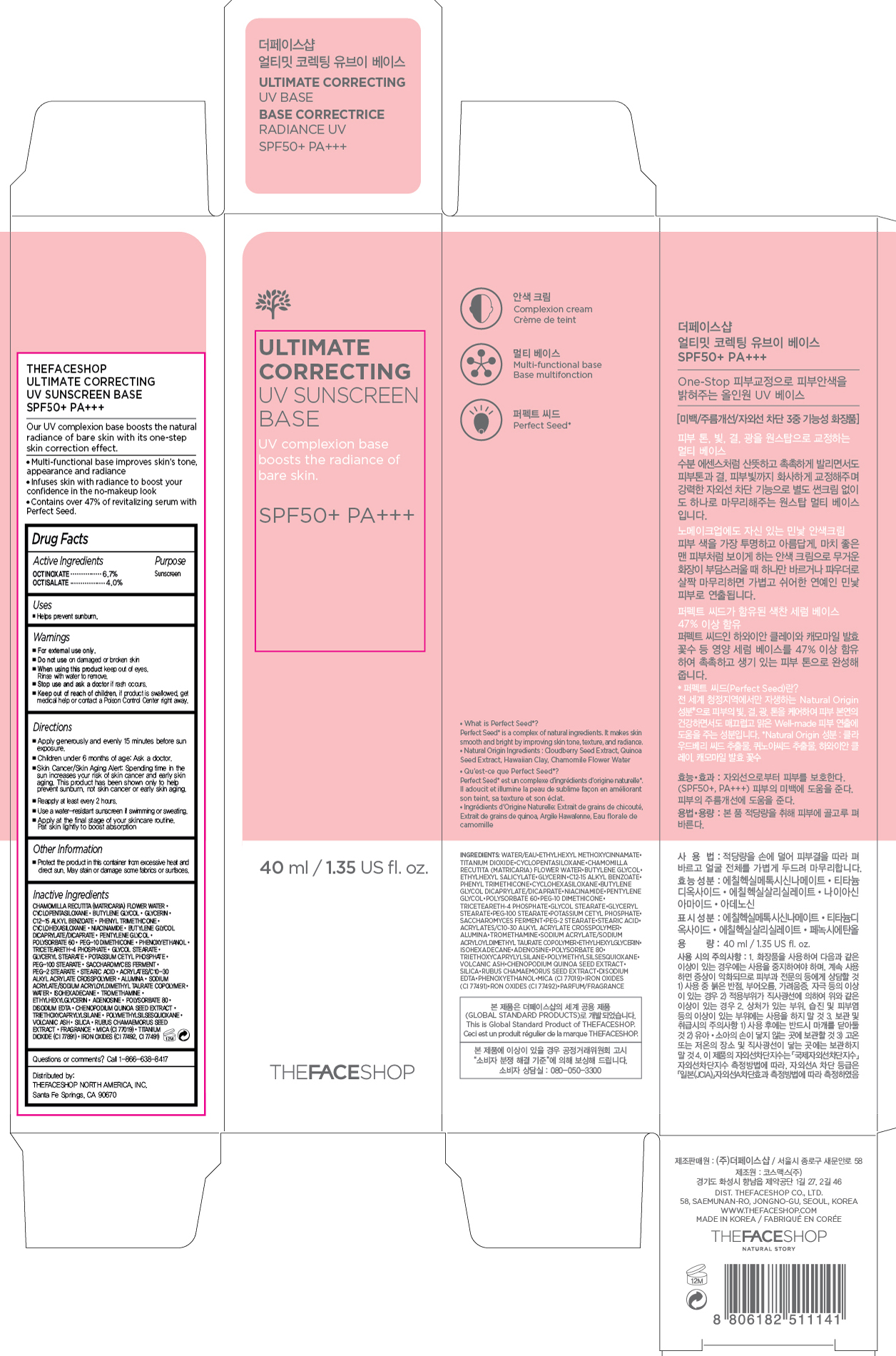 DRUG LABEL: ULTIMATE CORRECTING
NDC: 51523-393 | Form: CREAM
Manufacturer: THEFACESHOP CO., LTD.
Category: otc | Type: HUMAN OTC DRUG LABEL
Date: 20150928

ACTIVE INGREDIENTS: OCTISALATE 1.6 g/40 mL; OCTINOXATE 2.68 g/40 mL
INACTIVE INGREDIENTS: WATER

ULTIMATE CORRECTING UV SUSNCREEN BASE SPF50+ PA+++ 34200393

Active Ingredients:

Octinoxate 6.7 %

Octisalate 4.0 %

Purpose

Sunscreen

Sunscreen

Uses:

Helps prevent sunburn.

Warnings:

For external use only.

Do not use on damaged or broken skin

When using this product keep out of eyes. Rinse with water to remove.

Stop use and ask a doctor if rash occurs.

Keep out of reach of children. If product is swallowed, get medical help or contact a Poison Control Center right away.

Directions:

Apply generously and evenly 15 minutes before sun exposure.
Children under 6 months of age: Ask a doctor.
Skin Cancer/Skin Aging Alert: Spending time in the sun increases your risk of skin cancer and early skin aging. This product has been shown only to help prevent sunburn, not skin cancer or early skin aging.
Reapply at least every 2 hours.
Use a water-resistant sunscreen if swimming or sweating.

Apply at the final step of your skincare routine. Pat skin lightly to boost absorption.

OTHER SAFETY INFORMATION

Protect the product in this container from excessive heat and direct sun.

May stain or damage some fabrics or surfaces.

Inactive Ingredients:

Chamomilla Recutita (Matricaria) Flower Water, Cyclopentasiloxane, Butylene Glycol, Glycerin, C12-15 Alkyl Benzoate, Phenyl Trimethicone, Cyclohexasiloxane, Niacinamide, Butylene Glycol Dicaprylate/Dicaprate, Pentylene Glycol, Polysorbate 60, PEG-10 Dimethicone, Phenoxyethanol, Triceteareth-4 Phosphate, Glycol Stearate, Glyceryl Stearate, Potassium Cetyl Phosphate, PEG-100 Stearate, Saccharomyces Ferment, PEG-2 Stearate, Stearic Acid, Acrylates/C10-30 Alkyl Acrylate Crosspolymer, Alumina, Sodium Acrylate/Sodium Acryloyldimethyl Taurate Copolymer, Water, Isohexadecane, Tromethamine, Ethylhexylglycerin, Adenosine, Polysorbate 80, Disodium EDTA, Chenopodium Quinoa Seed Extract, Triethoxycaprylylsilane, Polymethylsilsesquioxane, Volcanic Ash, Silica, Rubus Chamaemorus Seed Extract, Fragrance, Mica (CI 77019), Titanium Dioxide (CI 77891), Iron Oxides (CI 77492, CI 77491)

Questions or comments? Call 1-866-638-8417

Distributed by:

THEFACESHOP NORTH AMERICA, INC.

Santa Fe Springs, CA 90670

PACKAGE LABEL

ULTIMATE CORRECTING

UV SUNSCREEN BASE

SPF50+ PA+++

Our UV complexion base boosts the natural radiance of bare skin with its one-step skin correction effect.

Multi-functional base improves skin's tone, appearance and radiance.

Infuses skin with radiance to boost your confidence in the no-makeup look.

Contains over 47% of revitalizing serum with Perfect Seed.